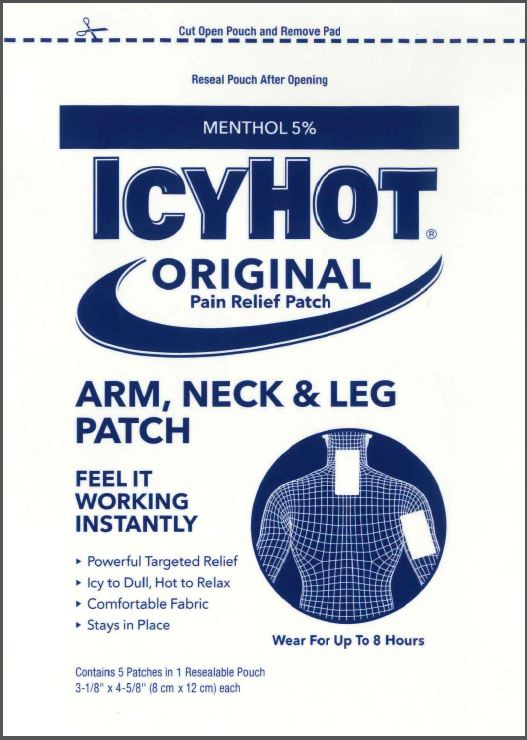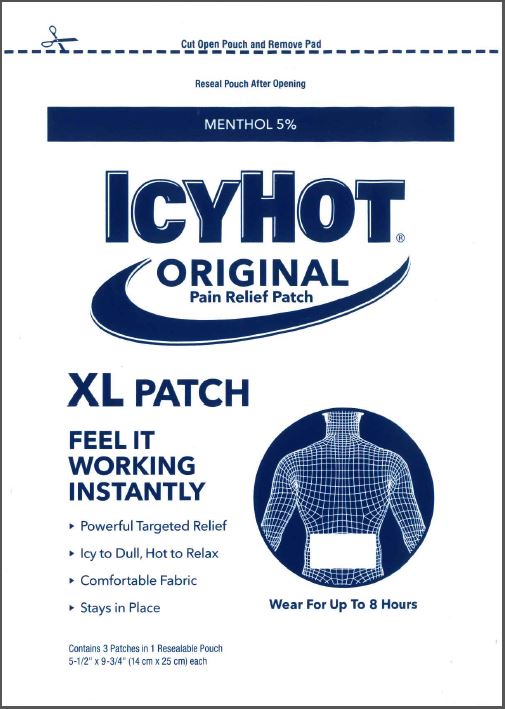 DRUG LABEL: Icy Hot
NDC: 62168-0084 | Form: PATCH
Manufacturer: Lead Chemical Co., Ltd.
Category: otc | Type: HUMAN OTC DRUG LABEL
Date: 20250421

ACTIVE INGREDIENTS: MENTHOL, UNSPECIFIED FORM 205.5 mg/1 1
INACTIVE INGREDIENTS: ALUMINUM HYDROXIDE; CARBOXYMETHYLCELLULOSE SODIUM, UNSPECIFIED; GLYCERIN; ISOPROPYL MYRISTATE; NONOXYNOL-30; POLYACRYLIC ACID (250000 MW); POLYSORBATE 80; SODIUM POLYACRYLATE (2500000 MW); SORBITAN SESQUIOLEATE; TALC; TARTARIC ACID; TITANIUM DIOXIDE; WATER

Icy Hot® Medicated Patch

Active Ingredient

Icy Hot Arm, Neck and Leg Patches; and Icy Hot XL Patches

Menthol 5%

Purpose

Topical analgesic

Uses

Icy Hot Arm, Neck and Leg Patches; and Icy Hot XL Patches

temporarily relieves minor pain associated with:

- arthritis
- simple backache
- bursitis
- tendonitis
- muscle strains
- sprains
- bruises
- cramps

Warnings

For external use only

When using this product

Icy Hot Arm, Neck and Leg Patches; and Icy Hot XL Patches

- use only as directed. Read and follow all directions and warnings on this label.
- avoid contact with eyes and mucous membranes
- rare cases of serious burns have been reported with products of this type
- do not apply to wounds or damaged, broken or irritated skin
- do not bandage tightly or apply local heat (such as heating pads) to the area of use
- a transient burning sensation may occur upon application but generally disappears in several days

Stop use and ask a doctor if

Icy Hot Arm, Neck and Leg Patches; and Icy Hot XL Patches

- condition worsens
- redness is present
- irritation develops
- symptoms persist for more than 7 days or clear up and occur again within a few days
- you experience signs of skin injury, such as pain, swelling, or blistering where the product was applied

If pregnant or breast-feeding,

ask a health professional before use.

Keep out of reach of children.

If swallowed, get medical help or contact a Poison Control Center right away.

Directions

Icy Hot Arm, Neck and Leg Patches; and Icy Hot XL Patches

adults and children over 12 years:

- remove backing from patch by firmly grasping both ends and gently pulling until backing separates in middle
- carefully remove smaller portion of backing from patch and apply exposed portion of patch to affected area
- once exposed portion of patch is positioned, carefully remove remaining backing to completely apply patch to affected area
- wear one Icy Hot patch for up to 8 hours
- repeat as necessary, but no more than 3 times daily

children 12 years or younger: ask a doctor

Inactive ingredients

Icy Hot Arm, Neck and Leg Patches; and Icy Hot XL Patches

aluminum hydroxide, cellulose gum, glycerin, isopropyl myristate, methyl acrylate/2-ethylhexyl acrylate copolymer, nonoxynol-30, polyacrylic acid, polysorbate 80, sodium polyacrylate, sorbitan sesquioleate, starch/acrylic acid graft copolymer sodium salt, talc, tartaric acid, titanium dioxide, water

Principal Display Panel - Arm, Neck & Leg Pouch

MENTHOL 5%

ICY HOT®
ORIGINAL
Pain Relief Patch

ARM, NECK & LEG
PATCH

FEEL IT
WORKING
INSTANTLY

- Powerful Targeted Relief
- Icy to Dull, Hot to Relax
- Comfortable Fabric
- Stays in Place

Wear For Up To 8 Hours

Contains 5 Patches in 1 Resealable Pouch
3-1/8" x 4-5/8" (8 cm x 12 cm) each

CHATTEM®
A SANOFI COMPANY
Dist. by Chattem, Inc., a Sanofi Company
P.O. Box 2219
Chattanooga, TN 37409-0219 USA
©2020 www.icyhot.com

Pouch Label - Arm, Neck, & Leg

Principal Display Panel - XL Back

MENTHOL 5%

ICY HOT®
ORIGINAL
Pain Relief Patch

XL PATCH

FEEL IT
WORKING
INSTANTLY

- Powerful Targeted Relief
- Icy to Dull, Hot to Relax
- Comfortable Fabric
- Stays in Place

Wear For Up To 8 Hours

Contains 3 Patches in 1 Resealable Pouch
5-1/2" x 9-3/4" (14 cm x 25 cm) each

CHATTEM®
A SANOFI COMPANY
Dist. by Chattem, Inc., a Sanofi Company
P.O. Box 2219
Chattanooga, TN 37409-0219 USA
©2020 www.icyhot.com

Pouch Label - XL Back